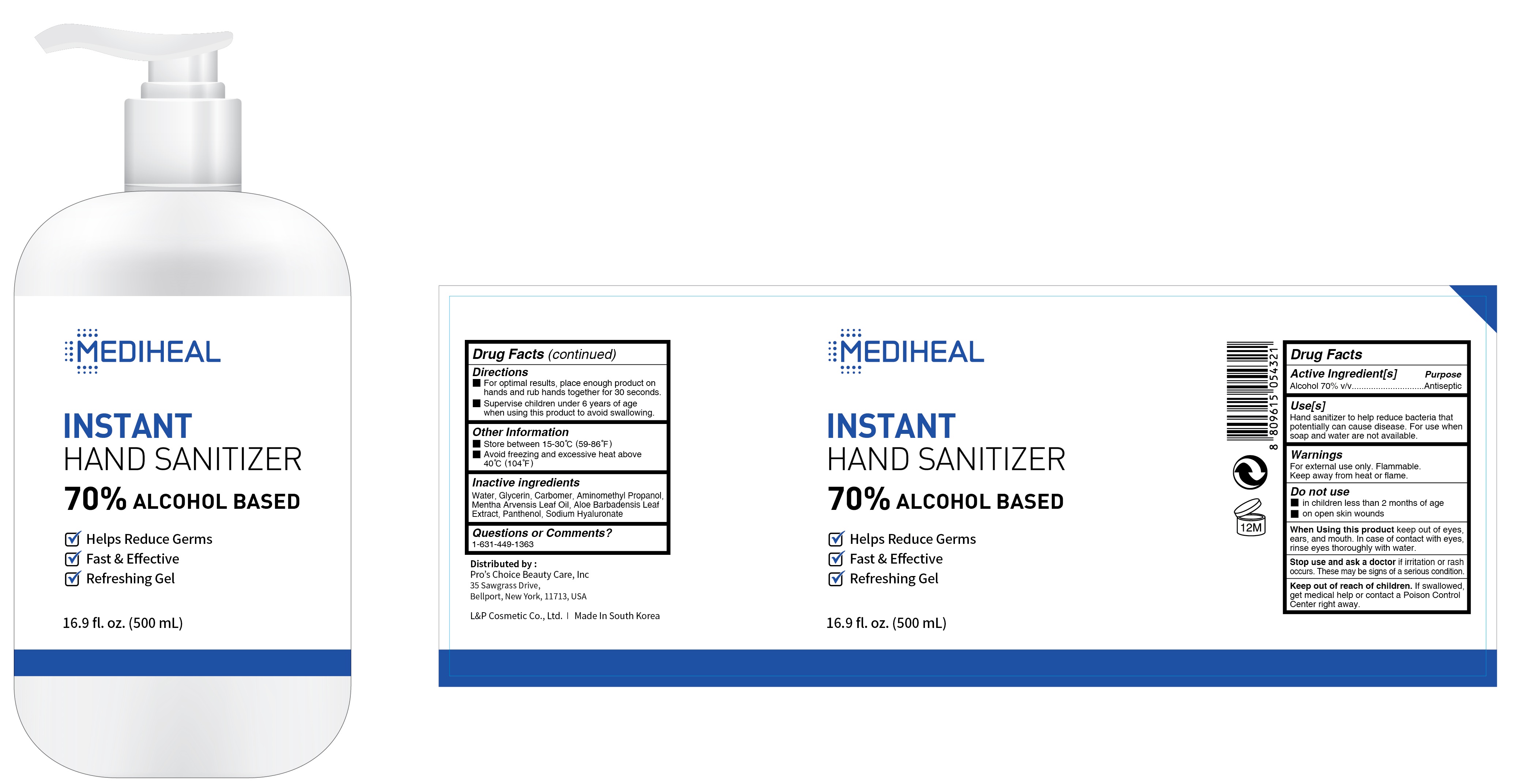 DRUG LABEL: MEDIHEAL INSTANT HAND SANITIZER
NDC: 74005-020 | Form: GEL
Manufacturer: L&P Cosmetic Co., Ltd.
Category: otc | Type: HUMAN OTC DRUG LABEL
Date: 20200511

ACTIVE INGREDIENTS: Alcohol 350 g/500 mL
INACTIVE INGREDIENTS: Water; Glycerin; CARBOMER HOMOPOLYMER, UNSPECIFIED TYPE; AMINOMETHYLPROPANOL; Mentha Arvensis Leaf Oil; .ALPHA.-TOCOPHEROL ACETATE; Panthenol; HYALURONATE SODIUM; ALOE VERA LEAF

ACTIVE INGREDIENT

Active ingredients: ALCOHOL 70.0% v/v

PURPOSE

Purpose: ANTISEPTIC

WARNINGS

For external use only. Flammable. Keep away from heat or flame
--------------------------------------------------------------------------------------------------------
Do not use
• in children less than 2 months of age
• on open skin wounds
--------------------------------------------------------------------------------------------------------
When using this product keep out of eyes, ears, and mouth. In case of contact with eyes, rinse eyes thoroughly with water.
--------------------------------------------------------------------------------------------------------
Stop use and ask a doctor if irritation or rash occurs. These may be signs of a serious condition.

Keep out of reach of children. If swallowed, get medical help or contact a Poison Control Center right away.

Uses

Hand sanitizer to help reduce bacteria that potentially can cause disease. For use when soap and water are not available.

Directions

• For optimal results, place enough product on hands and rub hands together for 30 seconds.
• Supervise children under 6 years of age when using this product to avoid swallowing.

Other information

• Store between 15-30C (59-86F)
• Avoid freezing and excessive heat above 40C (104F)

INACTIVE INGREDIENT

Inactive ingredients:

Water, Glycerin, Carbomer, Aminomethyl Propanol, Mentha Arvensis Leaf Oil, Tocopheryl Acetate, Panthenol, Sodium Hyaluronate, Aloe Barbadensis Leaf Extract